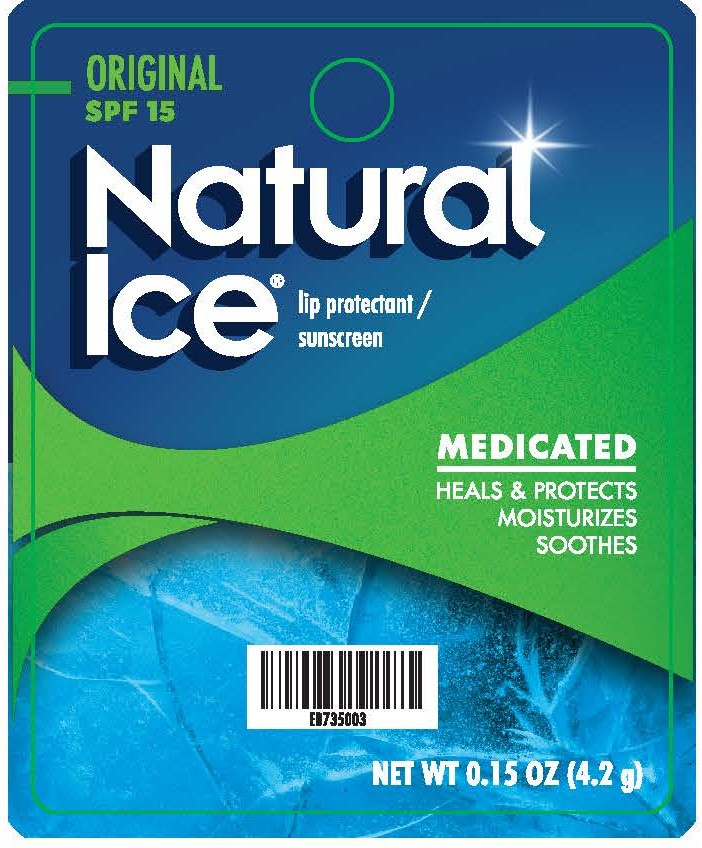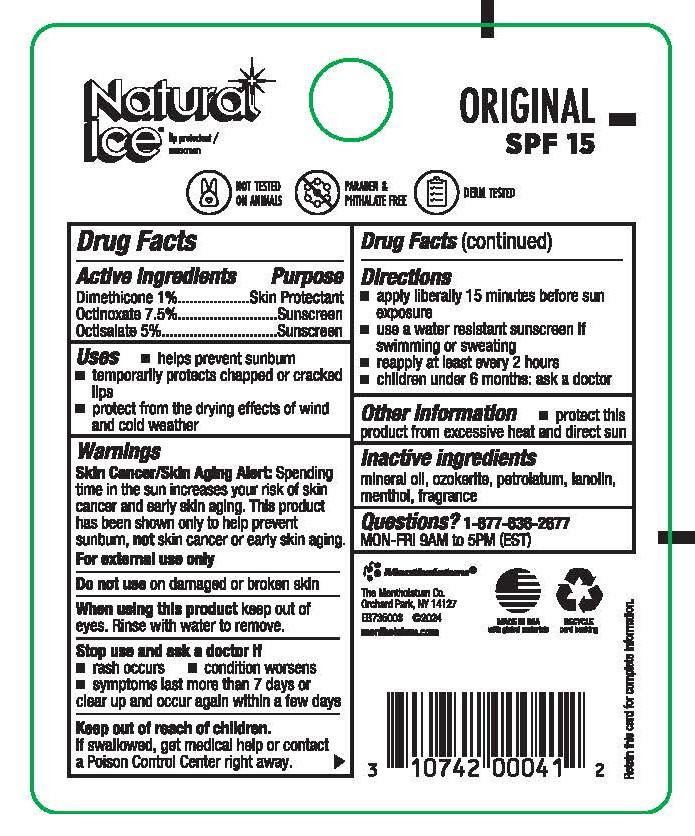 DRUG LABEL: Mentholatum Natural Ice - Original, SPF 15
NDC: 10742-3070 | Form: STICK
Manufacturer: The Mentholatum Company
Category: otc | Type: HUMAN OTC DRUG LABEL
Date: 20250619

ACTIVE INGREDIENTS: OCTISALATE 50 mg/1 g; DIMETHICONE 10 mg/1 g; OCTINOXATE 75 mg/1 g
INACTIVE INGREDIENTS: MINERAL OIL; LANOLIN; MENTHOL; PETROLATUM; FRAGRANCE 13576; CERESIN

Mentholatum Natural Ice - Original, SPF 15

Active ingredients

Dimethicone 1%
Octinoxate 7.5%
Octisalate 5%

Purpose

Dimethicone - Skin protectant

Octinoxate - Sunscreen

Octisalate - Sunscreen

Uses

- helps prevent sunburn
- temporarily protects chapped or cracked lips
- protect from the drying effects of wind and cold weather

Warnings

Skin Cancer/Skin Aging Alert: Spending time in the sun increases your risk of skin cancer and early skin aging. This product has been shown only to help prevent sunburn, not skin cancer or early skin aging.

For external use only

Do not use

on damaged or broken skin

When using this product

keep out of eyes. Rinse with water to remove.

Stop use and ask a doctor if

- rash occurs
- condition worsens
- symptoms last more than 7 days or clear up and occur again within a few days

Keep out of reach of children

If swallowed, get medical help or contact a Poison Control Center right away.

Directions

- apply liberally 15 minutes before sun exposure
- use a water resistant sunscreen if swimming or sweating
- reapply at least every 2 hours
- children under 6 months: ask a doctor

Inactive ingredients

mineral oil, ozokerite, petrolatum, lanolin, fragrance, menthol

Questions?

1-877-636-2677

MON-FRI 9AM to 5PM (EST)

mentholatum.com

Uses

- protects from the drying effects of wind and cold weather

Other Information

- protect this product from excessive heat and direct sun